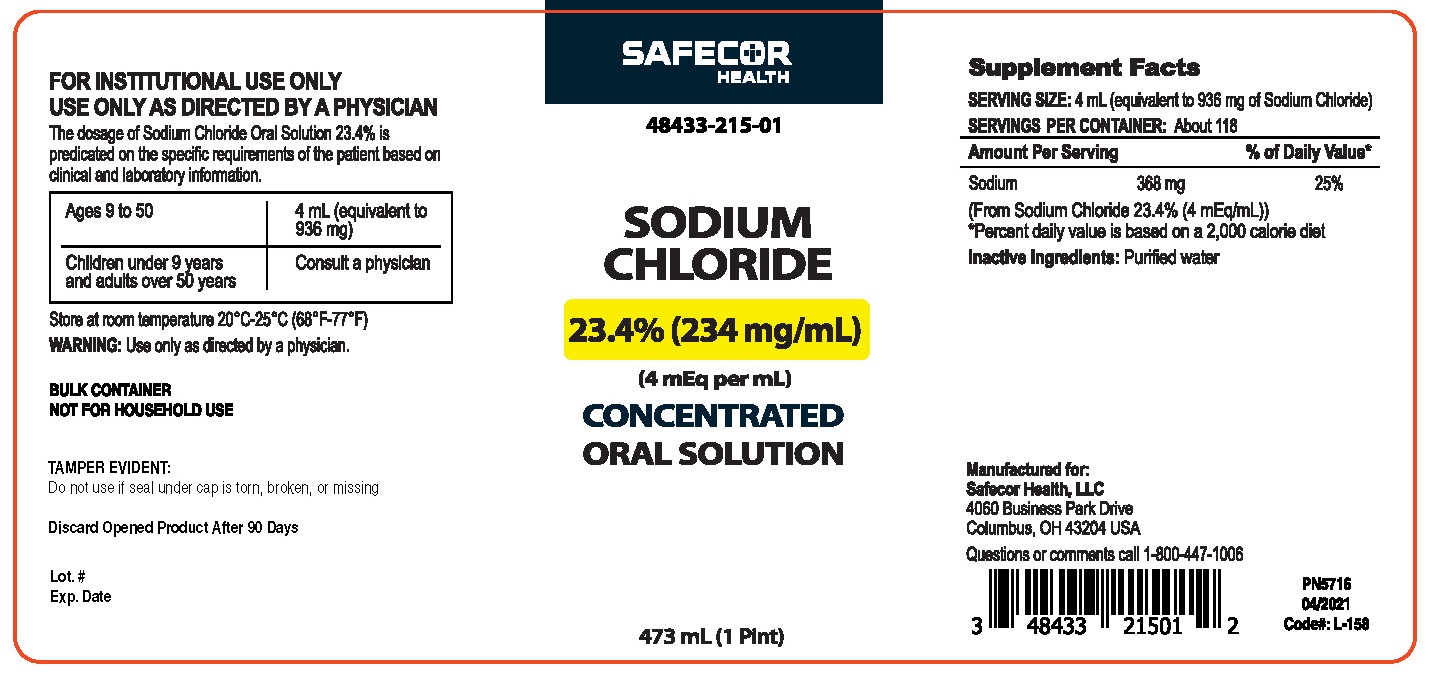 DRUG LABEL: SODIUM CHLORIDE
NDC: 48433-215 | Form: SOLUTION, CONCENTRATE
Manufacturer: Safecor Health, LLC
Category: other | Type: DIETARY SUPPLEMENT
Date: 20211209

ACTIVE INGREDIENTS: SODIUM CHLORIDE 936 mg/4 mL
INACTIVE INGREDIENTS: WATER

Sodium Chloride 23.4% Oral Solution

Statement of Identity

Safecor Health, LLC
4060 Business Park Drive
Columbus, OH 43204 USA

SODIUM CHLORIDE

23.4% (234 mg/ml)
(4 mEq per ml)
CONCENTRATED
ORAL SOLUTION

FOR INSTITUTIONAL USE ONLY USE ONLY AS DIRECTED BY A PHYSICIAN

The dosage of Sodium Chloride Oral Solution 23.4% is predicated on the specific requirements of the patient based on clinical and laboratory information.

Ages 9 to 50 | 4 ml (equivalent to 936 mg)
Children under 9 years and adults over 50 years | Consult a physician

Supplement Facts
SERVING SIZE: 4 ml (equivalent to 936 mg of Sodium Chloride)
SERVINGS PER CONTAINER: About 118

Amount Per Serving | % of Daily Value*
Sodium 368 | 25%

(From Sodium Chloride 23.4% (4 mEq/ml))
*Percent daily value is based on a 2,000 calorie diet
Inactive Ingredients: Purified water

WARNING:

Use only as directed by a physician.

BULK CONTAINER
NOT FOR HOUSEHOLD USE

TAMPER EVIDENT:
Do not use if seal under cap is torn, broken, or missing

Discard Opened Product After 90 Days

PRINCIPAL DISPLAY PANEL - 473 ml (1 Pint) Bottle

FOR INSTITUTIONAL USE ONLY
USE ONLY AS DIRECTED BY A PHYSICIAN
The dosage of Sodium Chloride Oral Solution 23.4% is predicated on the specific requirements of the patient based on clinical and laboratory information.

Ages 9 to 50 | 4 ml (equivalent to 936 mg)
Children under 9 years and adults over 50 years | Consult a physician

Store at room temperature 20°C-25°C (68°F-77°F)

WARNING: Use only as directed by a physician.

BULK CONTAINER
NOT FOR HOUSEHOLD USE

TAMPER EVIDENT:
Do not use if seal under cap is torn, broken, or missing

Discard Opened Product After 90 Days

Lot. #
Exp.Date

SAFECOR
HEALTH
48433-215-01

SODIUM
CHLORIDE
23.4% (234 mg/ml)
(4 mEq per ml)
CONCENTRATED
ORAL SOLUTION
473 ml (1 Pint)

Supplement Facts
SERVING SIZE: 4 ml (equivalent to 936 mg of Sodium Chloride)
SERVINGS PER CONTAINER: About 118

Amount Per Serving | % of Daily Value*
Sodium 368 mg | 25%

(From Sodium Chloride 23.4% (4 mEq/ml))
*Percent daily value is based on a 2,000 calorie diet

Inactive Ingredients: Purified water

Manufactured for:
Safecor Health, LLC
4060 Business Park Drive
Columbus, OH 43204 USA
Questions or comments call 1-800-447-1006

PN5716
04/2021
Code#: L-158
3 48433 21501 2